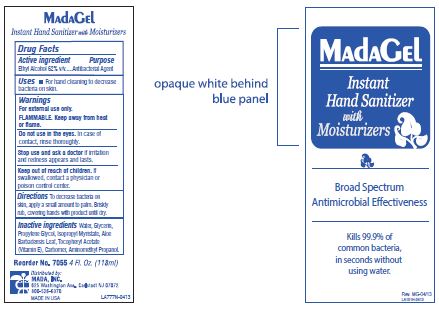 DRUG LABEL: Mada
NDC: 11928-004 | Form: GEL
Manufacturer: Mada Medical Products, Inc.
Category: otc | Type: HUMAN OTC DRUG LABEL
Date: 20241120

ACTIVE INGREDIENTS: ALCOHOL 62 mL/100 mL
INACTIVE INGREDIENTS: WATER; GLYCERIN; PROPYLENE GLYCOL; ISOPROPYL MYRISTATE; ALOE VERA LEAF; .ALPHA.-TOCOPHEROL ACETATE; CARBOXYPOLYMETHYLENE; AMINOMETHYLPROPANOL

11928-004 Mada

Active ingredient

Ethyl Alcohol 62% v/v

Purpose

Antibacterial Agent

Uses

For hand cleaning to decrease bacteria on skin.

Warnings

For external use only.

FLAMMABLE Keep away from heat or flame.

Do not use in eyes.

In case of contact, rinse thoroughly.

Stop use and ask a doctor if irritation and redness appears and lasts.

Keep out of reach of children.

If swallowed, contact a physician or poison control center.

Directions

To decrease bacteria on skin, apply a small amount to palm.

Briskly rub,covering hands with product until dry.

Inactive ingredients

Water, Glycerin, Propylene Glycol, Isopropyl Myristate, Aloe Barbadensis Leaf, Tocopheryl Acetate, Carbomer, Aminomethyl Propanol

PACKAGE LABEL

MadaGel

Instant

Hand Sanitizer

with

Moisturizers

Broad Spectrum

Antimicrobial Effectiveness

Kills 99.9% of

common bacteria

in seconds without

using water.

4 Fl. Oz. (118ml)